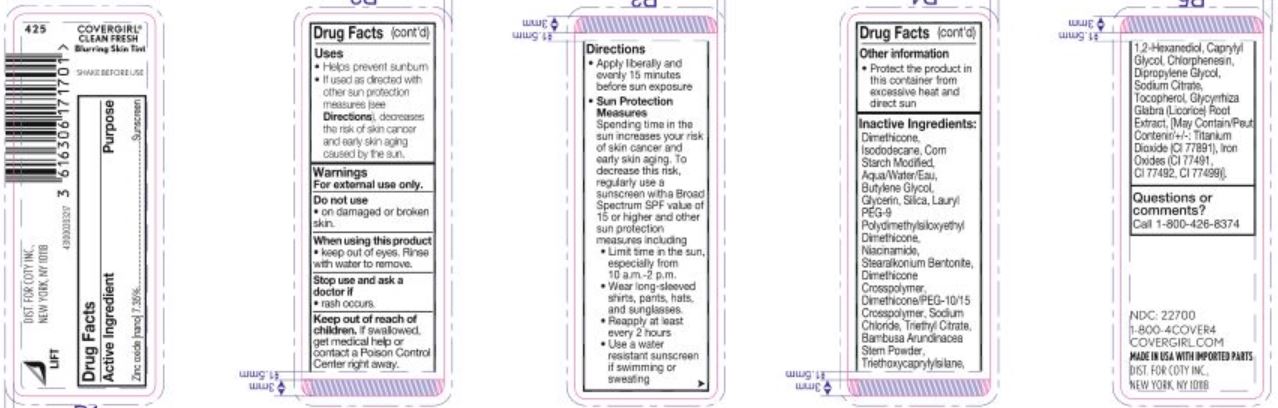 DRUG LABEL: Covergirl Clean Fresh Blurring Skintint SPF 30 Mineral Sunscreen Liquid Foundation- All shades
NDC: 22700-701 | Form: EMULSION
Manufacturer: Noxell
Category: otc | Type: HUMAN OTC DRUG LABEL
Date: 20251217

ACTIVE INGREDIENTS: ZINC OXIDE 73.5 mg/1 mL
INACTIVE INGREDIENTS: SILICON DIOXIDE; TRIETHOXYCAPRYLYLSILANE; BAMBUSA ARUNDINACEA STEM; DIMETHICONE/PEG-10/15 CROSSPOLYMER; SODIUM CITRATE; MODIFIED CORN STARCH (1-OCTENYL SUCCINIC ANHYDRIDE); DIPROPYLENE GLYCOL; WATER; CI 77491; CI 77499; ISODODECANE; CHLORPHENESIN; GLYCYRRHIZA GLABRA (LICORICE) ROOT; NIACINAMIDE; DIMETHICONE CROSSPOLYMER; STEARALKONIUM BENTONITE; SODIUM CHLORIDE; TRIETHYL CITRATE; CAPRYLYL GLYCOL; CI 77891; 1,2-HEXANEDIOL; DIMETHICONE; TOCOPHEROL; CI 77492; GLYCERIN; BUTYLENE GLYCOL; LAURYL PEG-9 POLYDIMETHYLSILOXYETHYL DIMETHICONE

Active ingredient

Zinc oxide 7.35%

Purpose

Sunscreen

Uses

- helps prevent sunburn
- if used as directed with other sun protection measures (see Directions), decreases the risk of skin cancer and early skin aging caused by the sun.

Warnings

For external use only

Do not use

on damaged or broken skin

When using this product

keep out of eyes. Rinse with water to remove.

Stop use and ask a doctor if

rash occurs

Keep out of reach of children.

If swallowed, get medical help or contact a Poison Control Center right away.

Directions

- apply liberally and evenly 15 minutes before sun exposure
- Sun Protection Measures Spending time in the sun increases your risk of skin cancer and early skin aging. To decrease this risk, regularly use a sunscreen witha Broad Spectrum SPF value of 15 or higher and other sun protection measures including • Limit time in the sun, especially from 10 a.m.-2 p.m. • Wear long-sleeved shirts, pants, hats, and sunglasses.
- Reapply at least every 2 hours
- Use a water resistant sunscreen if swimming or sweating

Other information

protect the product in this container from excessive heat and direct sun

Inactive ingredients

Dimethicone, Isododecane, Corn Starch Modiﬁed, Aqua/Water/Eau, Butylene Glycol, Glycerin, Silica, Lauryl PEG-9 Polydimethylsiloxyethyl Dimethicone, Niacinamide, Stearalkonium Bentonite, Dimethicone Crosspolymer, Dimethicone/PEG-10/15 Crosspolymer, Sodium Chloride, Triethyl Citrate, Bambusa Arundinacea Stem Powder, Triethoxycaprylylsilane, 1,2-Hexanediol, Caprylyl Glycol, Chlorphenesin, Dipropylene Glycol, Sodium Citrate, Tocopherol, Glycyrrhiza Glabra (Licorice) Root Extract, [May Contain/Peut Contenir/+/-: Titanium Dioxide (CI 77891), Iron Oxides (CI 77491, CI 77492, CI 77499)]

Questions or comments?

Call 1-800-426-8374